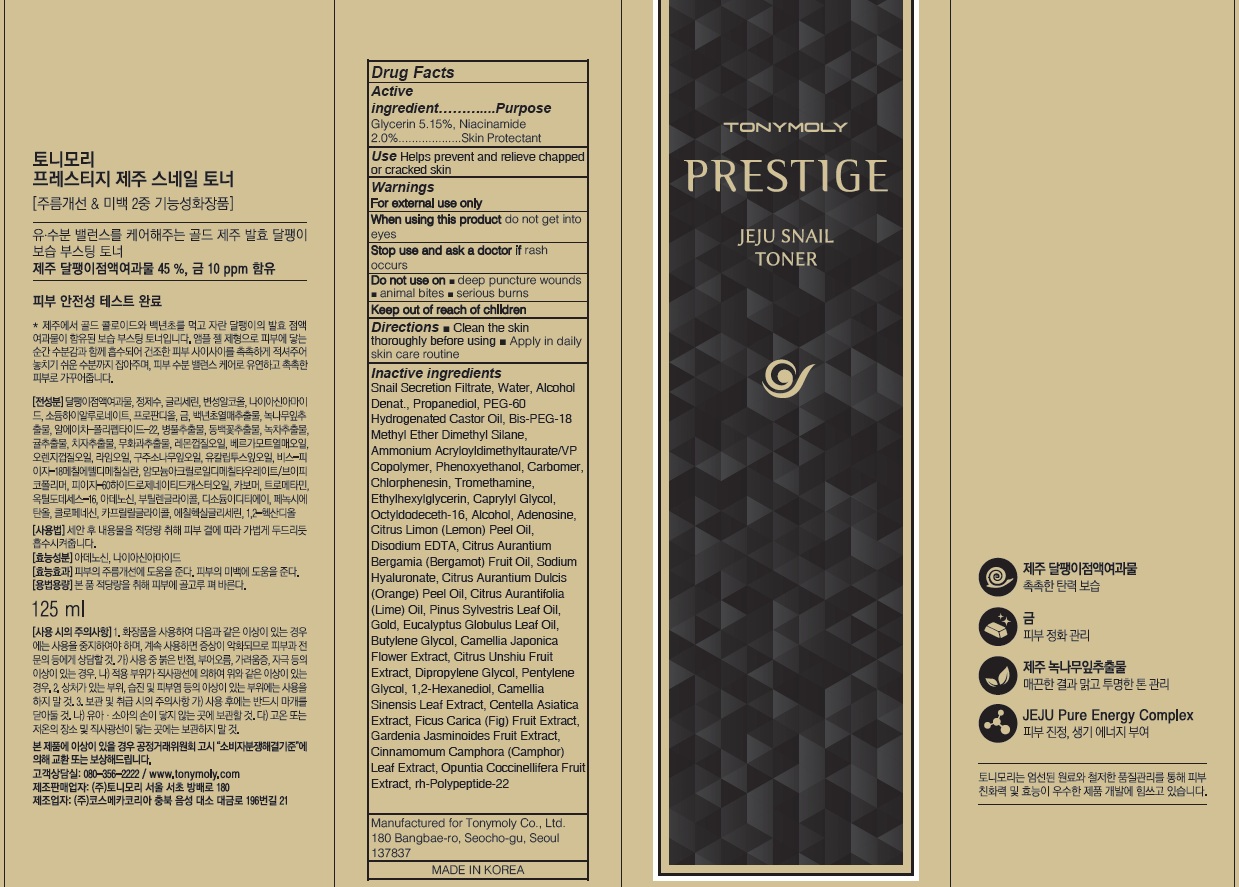 DRUG LABEL: PRESTIGE JEJU SNAIL TONER
NDC: 59078-320 | Form: LIQUID
Manufacturer: TONYMOLY CO.,LTD
Category: otc | Type: HUMAN OTC DRUG LABEL
Date: 20160729

ACTIVE INGREDIENTS: Glycerin 6.43 g/125 mL; Niacinamide 2.50 g/125 mL
INACTIVE INGREDIENTS: Water; Propanediol

ACTIVE INGREDIENT

Active Ingredient: Glycerin 5.15%, Niacinamide 2.0%

INACTIVE INGREDIENT

Inactive Ingredients: Snail Secretion Filtrate, Water, Alcohol Denat., Propanediol, PEG-60 Hydrogenated Castor Oil, Bis-PEG-18 Methyl Ether Dimethyl Silane, Ammonium Acryloyldimethyltaurate/VP Copolymer, Phenoxyethanol, Carbomer, Chlorphenesin, Tromethamine, Ethylhexylglycerin, Caprylyl Glycol, Octyldodeceth-16, Alcohol, Adenosine, Citrus Limon (Lemon) Peel Oil, Disodium EDTA, Citrus Aurantium Bergamia (Bergamot) Fruit Oil, Sodium Hyaluronate, Citrus Aurantium Dulcis (Orange) Peel Oil, Citrus Aurantifolia (Lime) Oil, Pinus Sylvestris Leaf Oil, Gold, Eucalyptus Globulus Leaf Oil, Butylene Glycol, Camellia Japonica Flower Extract, Citrus Unshiu Fruit Extract, Dipropylene Glycol, Pentylene Glycol, 1,2-Hexanediol, Camellia Sinensis Leaf Extract, Centella Asiatica Extract, Ficus Carica (Fig) Fruit Extract, Gardenia Jasminoides Fruit Extract, Cinnamomum Camphora (Camphor) Leaf Extract, Opuntia Coccinellifera Fruit Extract, rh-Polypeptide-22

PURPOSE

Purpose: Skin Protectant

WARNINGS

Warnings: For external use only When using this product do not get into eyes, Stop use and ask a doctor if rash occurs Do not use on - deep puncture wounds - animal bites - serious burns Keep out of reach of children

KEEP OUT OF REACH OF CHILDREN

Use

Use: Helps prevent and relieve chapped or cracked skin

Directions

Directions: - Clean the skin thoroughly before using - Apply in daily skin care routine